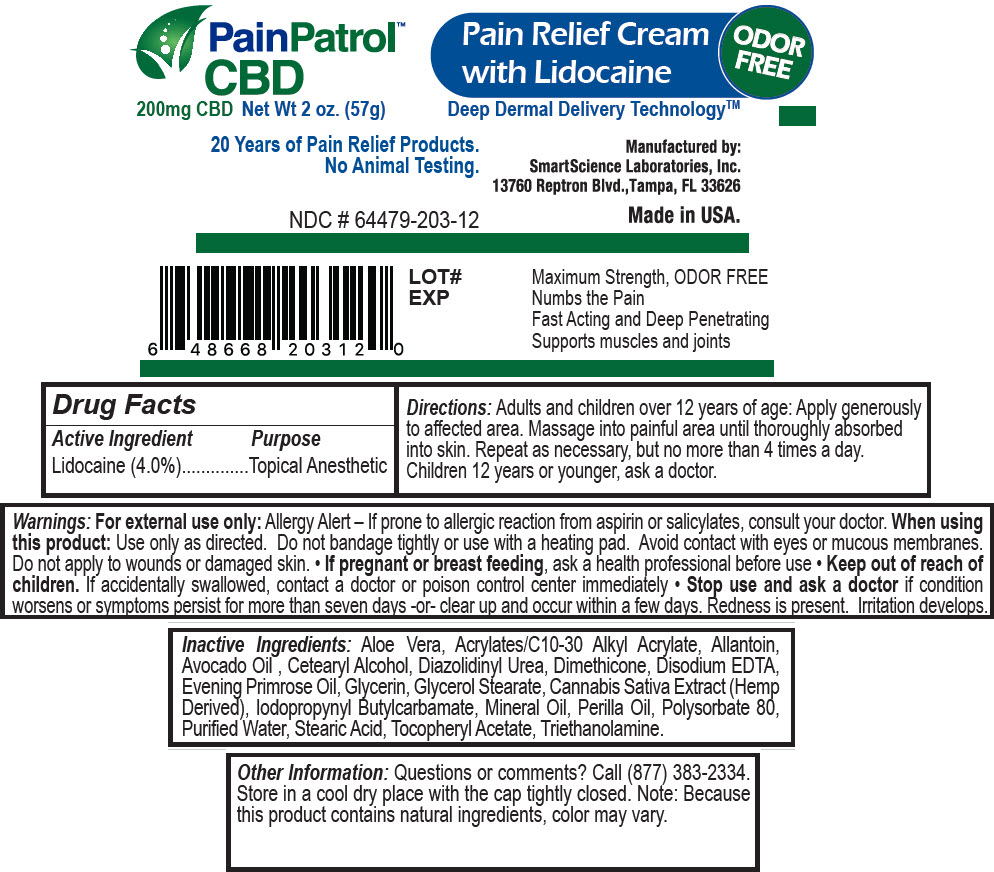 DRUG LABEL: PainPatrol CBD Pain Relief with Lidocaine
NDC: 64479-203 | Form: CREAM
Manufacturer: SmartScience Laboratories, Inc.
Category: otc | Type: HUMAN OTC DRUG LABEL
Date: 20200219

ACTIVE INGREDIENTS: LIDOCAINE HYDROCHLORIDE 4 mg/100 g
INACTIVE INGREDIENTS: ALOE VERA LEAF; CARBOMER INTERPOLYMER TYPE A (ALLYL SUCROSE CROSSLINKED); Allantoin; Avocado Oil; Cetyl Alcohol; Diazolidinyl Urea; Dimethicone; EDETATE DISODIUM ANHYDROUS; Evening Primrose Oil; Glycerin; GLYCERYL MONOSTEARATE; Cannabidiol; Iodopropynyl Butylcarbamate; Mineral Oil; Perilla Frutescens Seed Oil; Polysorbate 80; WATER; Stearic Acid; .ALPHA.-TOCOPHEROL ACETATE; TROLAMINE

PainPatrol™ CBD Pain Relief Cream with Lidocaine

Drug Facts

Active Ingredient

Lidocaine (4.0%)

Purpose

INDICATIONS AND USAGE

Topical Anesthetic

Warnings

For external use only:

Allergy Alert

If prone to allergic reaction from aspirin or salicylates, consult your doctor.

When using this product

Use only as directed. Do not bandage tightly or use with a heating pad. Avoid contact with eyes or mucous membranes. Do not apply to wounds or damaged skin.

PREGNANCY OR BREAST FEEDING

- If pregnant or breast feeding, ask a health professional before use

- Keep out of reach of children. If accidentally swallowed, contact a doctor or poison control center immediately

- Stop use and ask a doctor if condition worsens or symptoms persist for more than seven days -or- clear up and occur within a few days. Redness is present. Irritation develops.

Directions

Adults and children over 12 years of age: Apply generously to affected area. Massage into painful area until thoroughly absorbed into skin. Repeat as necessary, but no more than 4 times a day. Children 12 years or younger, ask a doctor.

Inactive Ingredients

Aloe Vera, Acrylates/C10-30 Alkyl Acrylate, Allantoin, Avocado Oil , Cetearyl Alcohol, Diazolidinyl Urea, Dimethicone, Disodium EDTA, Evening Primrose Oil, Glycerin, Glycerol Stearate, Cannabis Sativa Extract (Hemp Derived), Iodopropynyl Butylcarbamate, Mineral Oil, Perilla Oil, Polysorbate 80, Purified Water, Stearic Acid, Tocopheryl Acetate, Triethanolamine.

Other Information

Questions or comments?

Call (877) 383-2334.

STORAGE AND HANDLING

Store in a cool dry place with the cap tightly closed. Note: Because this product contains natural ingredients, color may vary.

Manufacterd by:
SmartScience Laboratories, Inc.
13760 Reptron Blvd., Tampa, FL 33626

PRINCIPAL DISPLAY PANEL - 57 g Jar Label

PainPatrol™
CBD

200mg CBD Net Wt 2 oz. (57g)

Pain Relief Cream
with Lidocaine

ODOR
FREE

Deep Dermal Delivery Technology™